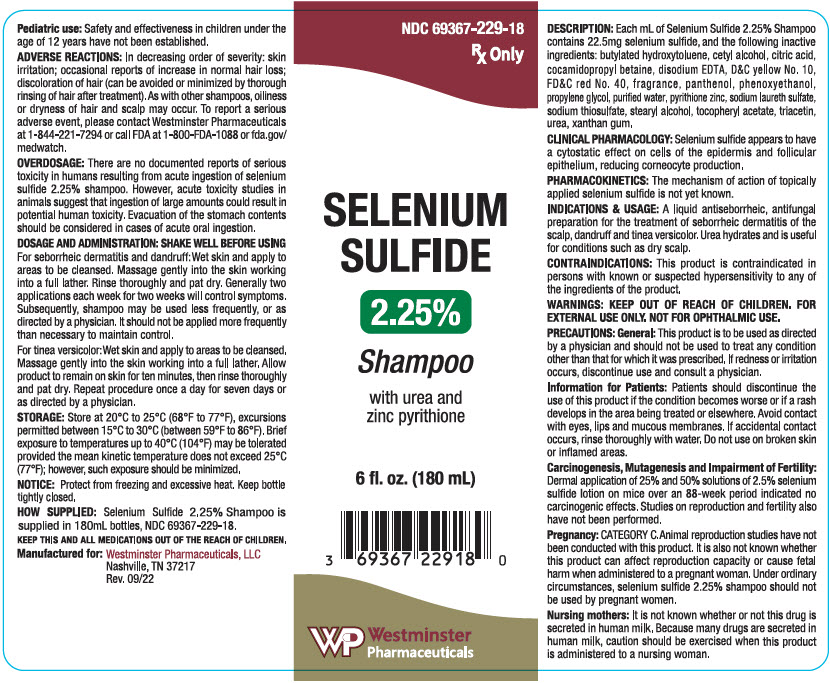 DRUG LABEL: Selenium Sulfide
NDC: 69367-229 | Form: SHAMPOO
Manufacturer: Westminster Pharmaceuticals, LLC
Category: prescription | Type: HUMAN PRESCRIPTION DRUG LABEL
Date: 20250423

ACTIVE INGREDIENTS: SELENIUM SULFIDE 22.5 mg/1 mL
INACTIVE INGREDIENTS: SODIUM LAURETH-3 SULFATE; .ALPHA.-TOCOPHEROL ACETATE; COCAMIDOPROPYL BETAINE; EDETATE DISODIUM; FD&C RED NO. 40; D&C YELLOW NO. 10; PANTHENOL; WATER; PYRITHIONE ZINC; UREA; XANTHAN GUM; BUTYLATED HYDROXYTOLUENE; CETYL ALCOHOL; SODIUM THIOSULFATE; STEARYL ALCOHOL; TRIACETIN; CITRIC ACID MONOHYDRATE; PROPYLENE GLYCOL; PHENOXYETHANOL

SELENIUM
SULFIDE
2.25%
Shampoo

DESCRIPTION

Each mL of Selenium Sulfide 2.25% Shampoo contains 22.5mg selenium sulfide, and the following inactive ingredients: butylated hydroxytoluene, cetyl alcohol, citric acid, cocamidopropyl betaine, disodium EDTA, D&C yellow No. 10, FD&C red No. 40, fragrance, panthenol, phenoxyethanol, propylene glycol, purified water, pyrithione zinc, sodium laureth sulfate, sodium thiosulfate, stearyl alcohol, tocopherol acetate, triacetin, urea, xanthan gum.

CLINICAL PHARMACOLOGY

Selenium sulfide appears to have a cytostatic effect on cells of the epidermis and follicular epithelium, reducing corneocyte production.

PHARMACOKINETICS

The mechanism of action of topically applied selenium sulfide is not yet known.

INDICATIONS & USAGE

A liquid antiseborrheic, antifungal preparation for the treatment of seborrheic dermatitis of the scalp, dandruff and tinea versicolor. Urea hydrates and is useful for conditions such as dry scalp.

CONTRAINDICATIONS

This product is contraindicated in persons with known or suspected hypersensitivity to any of the ingredients of the product.

WARNINGS

KEEP OUT OF REACH OF CHILDREN. FOR EXTERNAL USE ONLY. NOT FOR OPHTHALMIC USE.

PRECAUTIONS

General

This product is to be used as directed by a physician and should not be used to treat any condition other than that for which it was prescribed. If redness or irritation occurs, discontinue use and consult a physician.

Information for Patients

Patients should discontinue the use of this product if the condition becomes worse or if a rash develops in the area being treated or elsewhere. Avoid contact with eyes, lips and mucous membranes. If accidental contact occurs, rinse thoroughly with water. Do not use on broken skin or inflamed areas.

Carcinogenesis, Mutagenesis and Impairment of Fertility

Dermal application of 25% and 50% solutions of 2.5% selenium sulfide lotion on mice over an 88-week period indicated no carcinogenic effects. Studies on reproduction and fertility also have not been performed.

Pregnancy

CATEGORY C

Animal reproduction studies have not been conducted with this product. It is also not known whether this product can affect reproduction capacity or cause fetal harm when administered to a pregnant woman. Under ordinary circumstances, selenium sulfide 2.25% shampoo should not be used by pregnant women.

Nursing mothers

It is not known whether or not this drug is secreted in human milk. Because many drugs are secreted in human milk, caution should be exercised when this product is administered to a nursing woman.

Pediatric use

Safety and effectiveness in children under the age of 12 years have not been established.

ADVERSE REACTIONS

In decreasing order of severity: skin irritation; occasional reports of increase in normal hair loss; discoloration of hair (can be avoided or minimized by thorough rinsing of hair after treatment). As with other shampoos, oiliness or dryness of hair and scalp may occur. To report a serious adverse event, please contact Westminster Pharmaceuticals at 1-844-221-7294 or call FDA at 1-800-FDA-1088 or fda.gov/medwatch.

OVERDOSAGE

There are no documented reports of serious toxicity in humans resulting from acute ingestion of selenium sulfide 2.25% shampoo. However, acute toxicity studies in animals suggest that ingestion of large amounts could result in potential human toxicity. Evacuation of the stomach contents should be considered in cases of acute oral ingestion.

DOSAGE AND ADMINISTRATION

SHAKE WELL BEFORE USING

For seborrheic dermatitis and dandruff

Wet skin and apply to areas to be cleansed. Massage gently into the skin working into a full lather. Rinse thoroughly and pat dry. Generally two applications each week for two weeks will control symptoms. Subsequently, shampoo may be used less frequently, or as directed by a physician. It should not be applied more frequently than necessary to maintain control.

For tinea versicolor

Wet skin and apply to areas to be cleansed. Massage gently into the skin working into a full lather. Allow product to remain on skin for ten minutes, then rinse thoroughly and pat dry. Repeat procedure once a day for seven days or as directed by a physician.

STORAGE

Store at 20°C to 25°C (68°F to 77°F), excursions permitted between 15°C to 30°C (between 59°F to 86°F). Brief exposure to temperatures up to 40°C (104°F) may be tolerated provided the mean kinetic temperature does not exceed 25°C (77°F); however, such exposure should be minimized.

NOTICE: Protect from freezing and excessive heat. Keep bottle tightly closed.

HOW SUPPLIED

Selenium Sulfide 2.25% Shampoo is supplied in 180mL bottles, NDC 69367-229-18.

KEEP THIS AND ALL MEDICATIONS OUT OF THE REACH OF CHILDREN.

Manufactured for:
Westminster Pharmaceuticals, LLC
Nashville, TN 37217
Rev. 09/22

PRINCIPAL DISPLAY PANEL - 180 mL Bottle Label

NDC 69367-229-18

Rx Only

SELENIUM
SULFIDE

2.25%

Shampoo

with urea and
zinc pyrithione

6 fl. oz. (180 mL)

Westminster
Pharmaceuticals